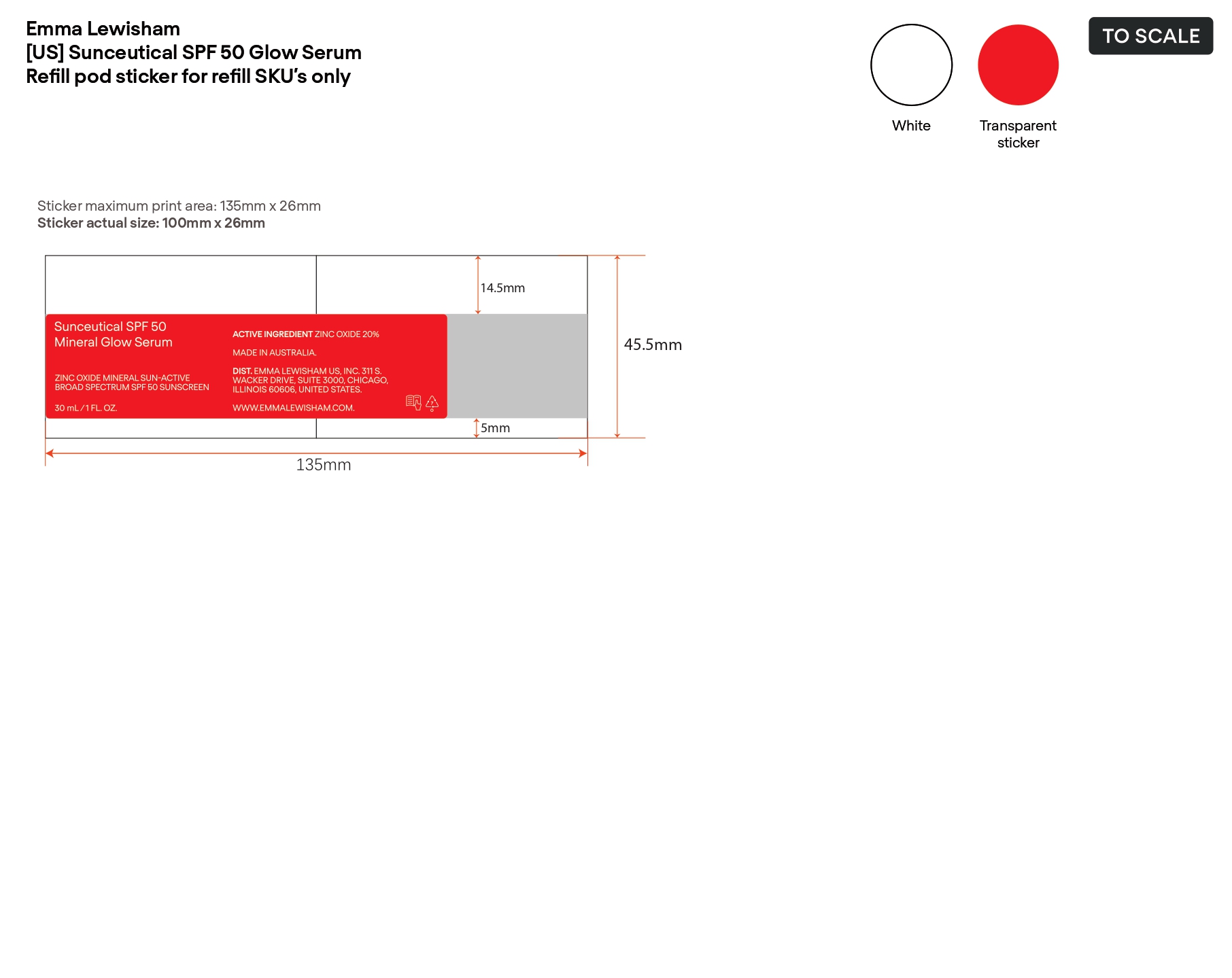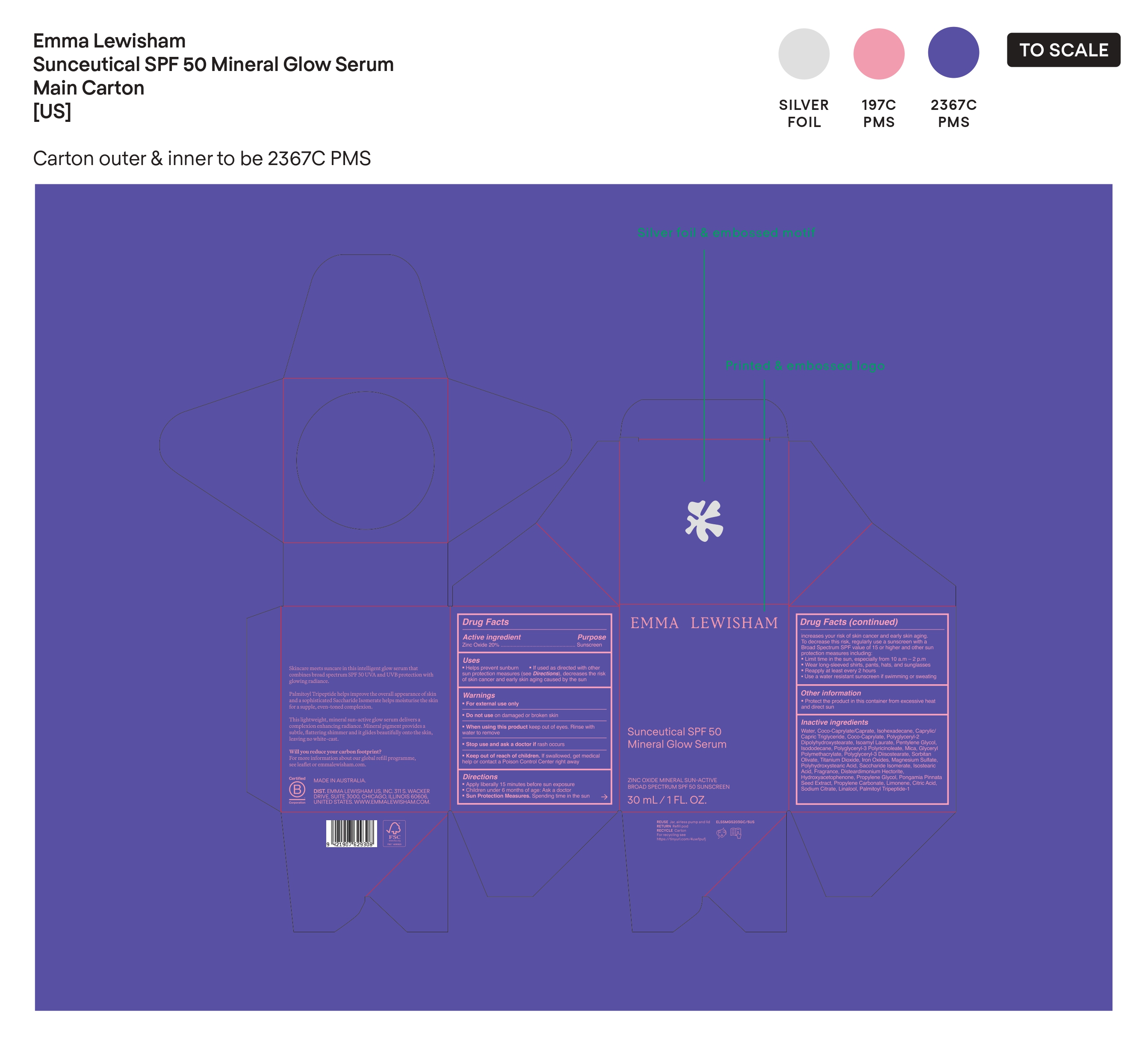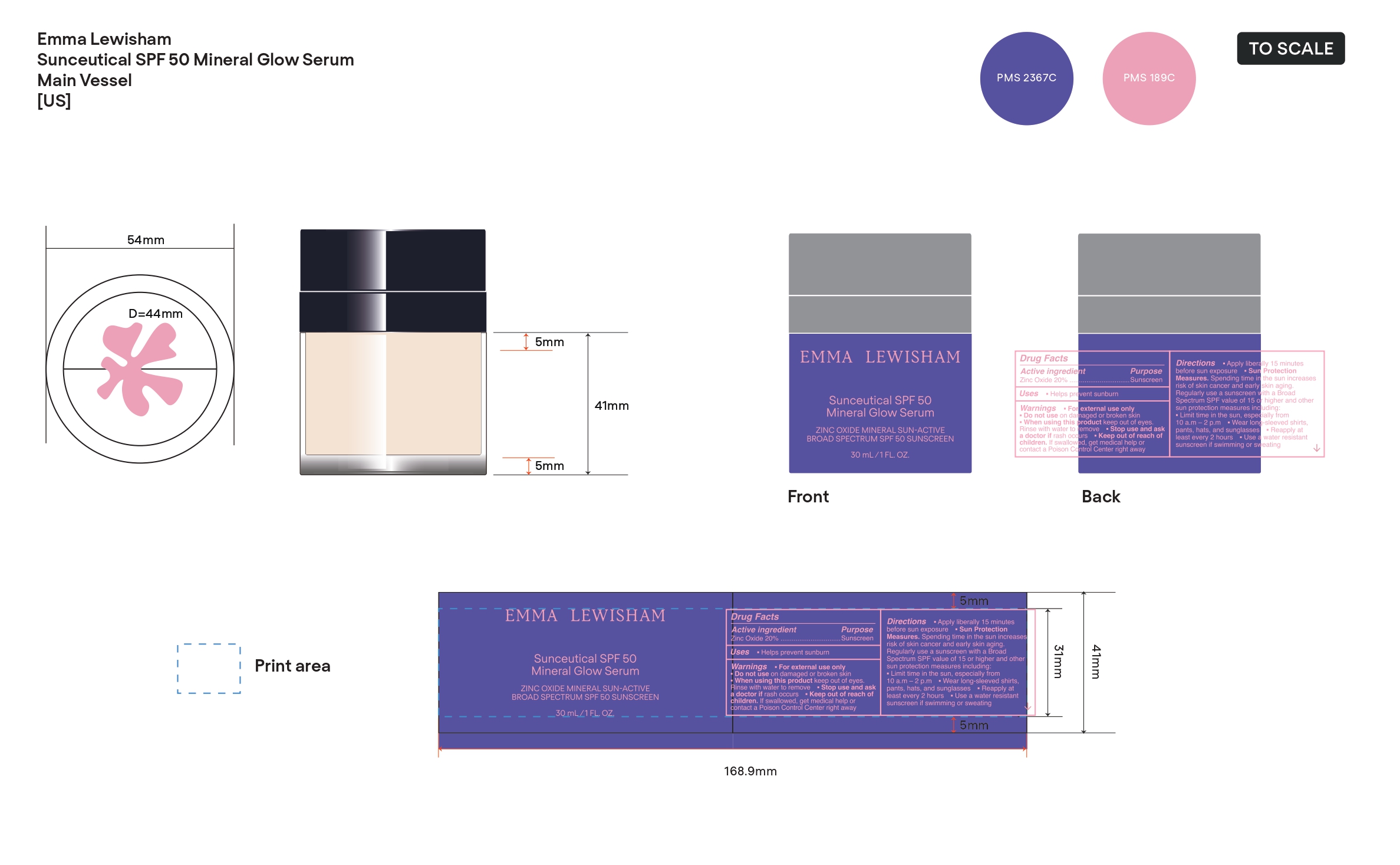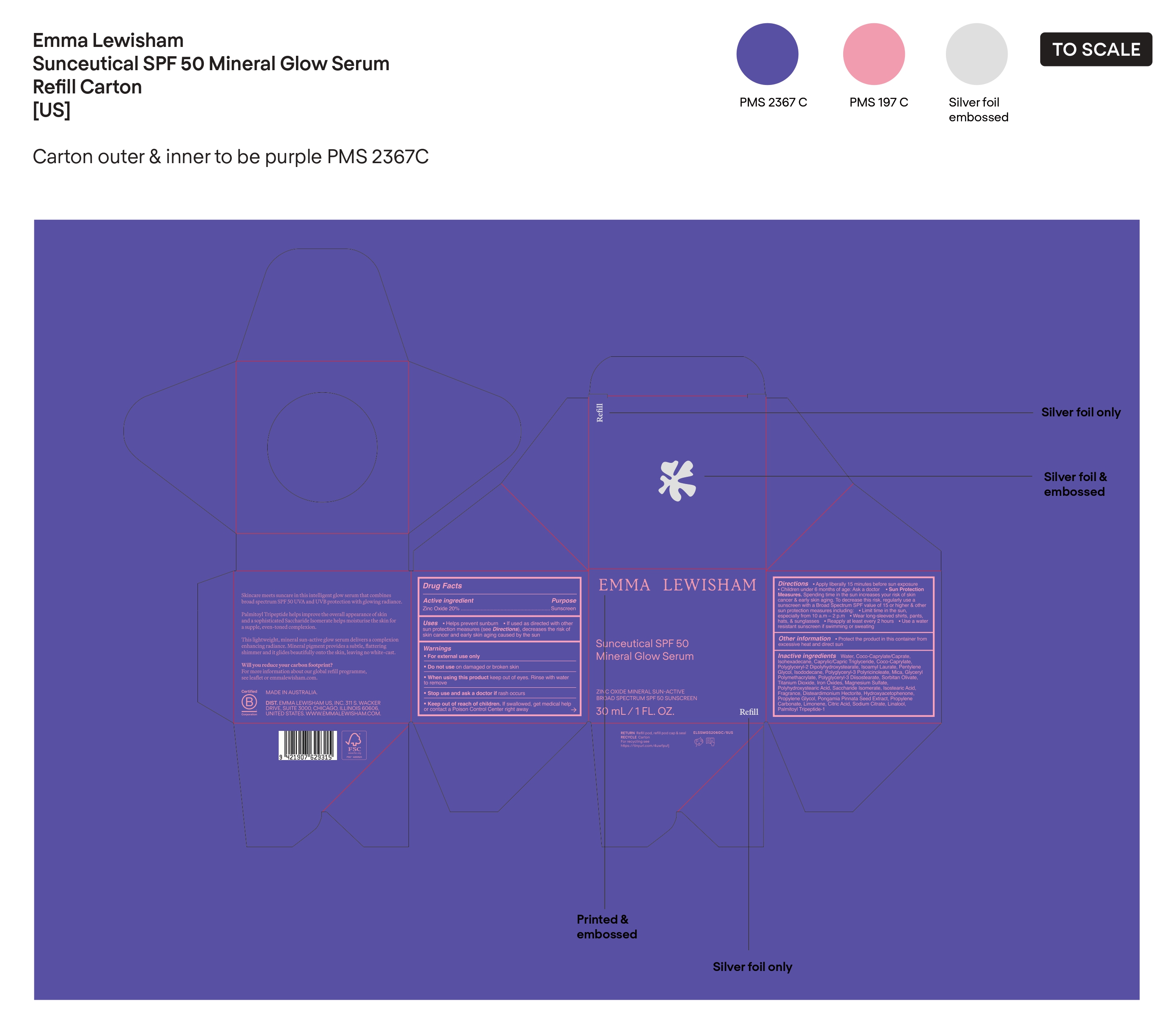 DRUG LABEL: EMMA LEWISHAM Sunceutical SPF 50 Mineral Glow Serum
NDC: 84981-002 | Form: LOTION
Manufacturer: EMMA LEWISHAM US, INC.
Category: otc | Type: HUMAN OTC DRUG LABEL
Date: 20250205

ACTIVE INGREDIENTS: ZINC OXIDE 20 g/100 mL
INACTIVE INGREDIENTS: WATER; HEXAMETHYLINDANOPYRAN; DISTEARDIMONIUM HECTORITE; PROPYLENE CARBONATE; COCO-CAPRYLATE/CAPRATE; CAPRYLIC/CAPRIC TRIGLYCERIDE; PONGAMIA PINNATA SEED; CITRIC ACID; ISOHEXADECANE; POLYGLYCERYL-2 DIPOLYHYDROXYSTEARATE; TITANIUM DIOXIDE; FERRIC OXIDE YELLOW; FERRIC OXIDE RED; MAGNESIUM SULFATE; ISOSTEARIC ACID; ISOCYCLEMONE E; LINALYL ACETATE; HYDROXYACETOPHENONE; PROPYLENE GLYCOL; LIMONENE, (+)-; PALMITOYL TRIPEPTIDE-1; COCO-CAPRYLATE; ISODODECANE; POLYGLYCERYL-3 PENTARICINOLEATE; MICA; SORBITAN OLIVATE; FERROSOFERRIC OXIDE; LINALOOL; ISOAMYL LAURATE; PENTYLENE GLYCOL; GLYCERYL POLYMETHACRYLATE (300000 MPA.S); POLYGLYCERYL-3 DIISOSTEARATE; POLYHYDROXYSTEARIC ACID (2300 MW); SACCHARIDE ISOMERATE; LEMON TERPENES; SODIUM CITRATE

Drug Facts

Active Ingredient

Zinc Oxide 20 %

Purpose

Sunscreen

Uses

•Helps prevent sunburn

• If used as directed with other sun protection measures (see Directions), decreases the risk of Skin cancer and early skin aging caused by the sun

Warnings

• For external use only

• Do not use on damaged or broken skin

• When using this product keep out of eyes. Rinse with water to remove

• Stop use and ask a doctor if rash occurs.

- Keep out of reach of children. If swallowed, get medical help or contact a Poison Control Center right away

Directions

• Apply liberally 15 minutes before sun exposure

• Children under 6 months of age: Ask a doctor

• Sun Protection Measures. Spending time in the sun increases your risk of skin cancer and early skin aging. To decrease this risk, regularly use a sunscreen with a Broad spectrum SPF value of 15 or higher and other sun protection measures including:

• Limit time in the sun, especially from 10 a.m. -2 p.m.

• Wear long-sleeved shirts, pants, hats, and sunglasses

• Reapply at least every 2 hours

•Use a water resistant sunscreen if swimming or sweating

Other information

• Protect the product in this container from excessive heat and direct sun

Inactive ingredients

Water, Coco-Caprylate/Caprate, Isohexadecane, Caprylic/ Capric Triglyceride, Coco-Caprylate, Polyglyceryl-2 Dipolyhydroxystearate, Isoamyl Laurate, Pentylene Glycol, Isododecane, Polyglyceryl-3 Polyricinoleate, Mica, Glyceryl Polymethacrylate, Polyglyceryl-3 Diisostearate, Sorbitan Olivate, Titanium Dioxide, Iron Oxides, Magnesium Sulfate, Polyhydroxystearic Acid, Saccharide Isomerate, Isostearic Acid, Fragrance, Disteardimonium Hectorite, Hydroxyacetophenone, Propylene Glycol, Pongamia Pinnata Seed Extract, Propylene Carbonate, Limonene, Citric Acid, Sodium Citrate, Linalool, Palmitoyl Tripeptide-1

PRINCIPAL DISPLYA PANEL

EMMA LEWISHAM

Sunceutical SPF 50 Mineral Glow Serum

ZINC OXIDE MINERAL SUN-ACTIVE

BROAD SPECTRUM SPF 50 SUNSCREEN

30 mL/1 FL. OZ.

PACKAGE LABEL

Sunceutical SPF 50 Mineral Glow Serum

ZINC OXIDE MINERAL SUN-ACTIVE

BROAD SPECTRUM SPF 50 SUNSCREEN

30 mL/1 FL. OZ.